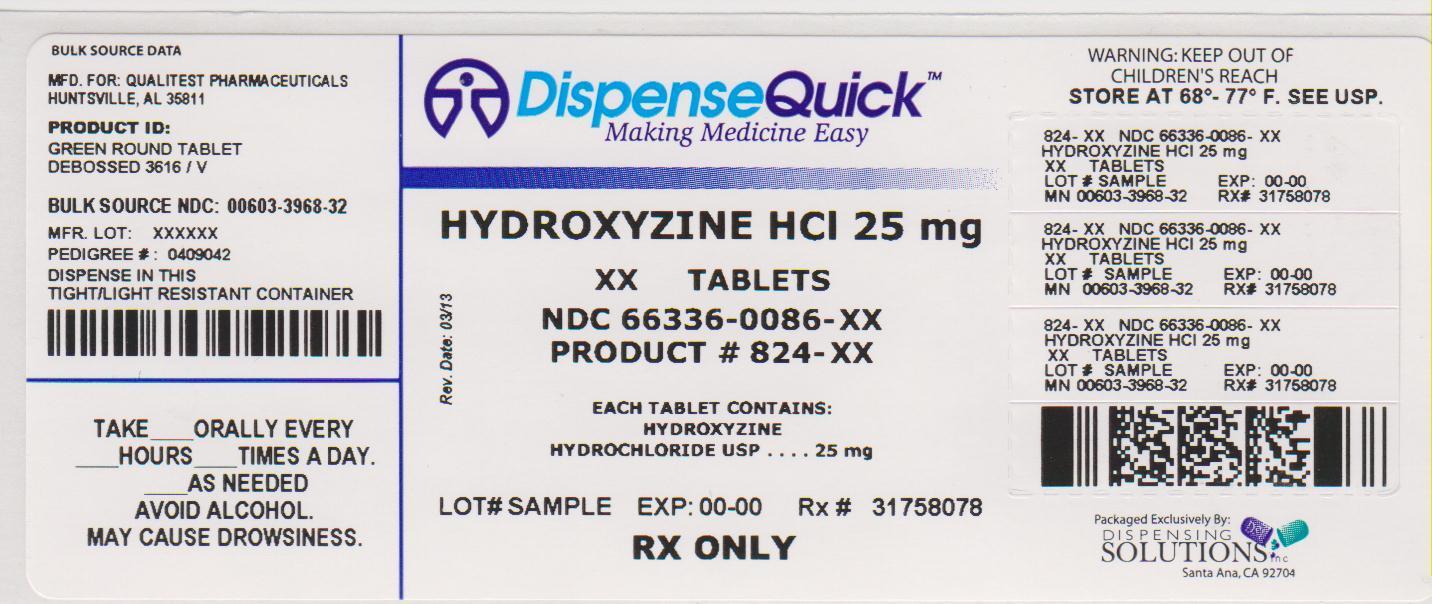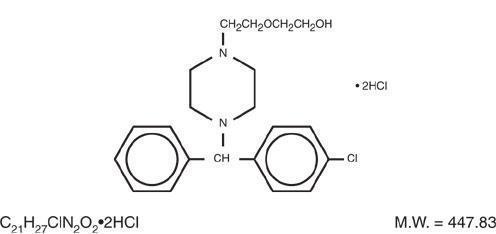 DRUG LABEL: Hydroxyzine Hydrochloride
NDC: 66336-086 | Form: TABLET, FILM COATED
Manufacturer: Dispensing Solutions, Inc.
Category: prescription | Type: HUMAN PRESCRIPTION DRUG LABEL
Date: 20130826

ACTIVE INGREDIENTS: HYDROXYZINE HYDROCHLORIDE 25 mg/1 1
INACTIVE INGREDIENTS: SILICON DIOXIDE; CALCIUM PHOSPHATE, DIBASIC, ANHYDROUS; HYPROMELLOSES; LACTOSE MONOHYDRATE; MAGNESIUM STEARATE; CELLULOSE, MICROCRYSTALLINE; POLYETHYLENE GLYCOLS; POVIDONES; SODIUM STARCH GLYCOLATE TYPE A POTATO; TITANIUM DIOXIDE; D&C YELLOW NO. 10; FD&C BLUE NO. 1

HYDROXYZINE HYDROCHLORIDE TABLETS, USP

Rx only

DESCRIPTION

Hydroxyzine hydrochloride has the chemical name of 2-[2-[4-(p-Chloro-α-phenylbenzyl)-1-piperazinyl]ethoxy]ethanol dihydrochloride.

Hydroxyzine hydrochloride occurs as a white, odorless powder which is very soluble in water.

Each tablet for oral administration contains 10 mg, 25 mg, or 50 mg hydroxyzine HCl. Inactive ingredients include colloidal silicon dioxide, dibasic calcium phosphate, hypromellose, lactose monohydrate, magnesium stearate, microcrystalline cellulose, polyethylene glycol, povidone, sodium starch glycolate, and titanium dioxide.

The 10 mg tablet also contains FD&C Red #40 Aluminum Lake and FD&C Yellow #6 Aluminum Lake. The 25 mg tablet also contains D&C Yellow #10 Aluminum Lake and FD&C Blue #1 Aluminum Lake. The 50 mg tablet also contains FD&C Red #40 Aluminum Lake and FD&C Yellow #5 Aluminum Lake.

CLINICAL PHARMACOLOGY

Hydroxyzine hydrochloride is unrelated chemically to the phenothiazines, reserpine, meprobamate or the benzodiazepines. Hydroxyzine is not a cortical depressant, but its action may be due to a suppression of activity in certain key regions of the subcortical area of the central nervous system.

Primary skeletal muscle relaxation has been demonstrated experimentally. Bronchodilator activity, and antihistaminic and analgesic effects have been demonstrated experimentally and confirmed clinically. An antiemetic effect, both by the apomorphine test and the veriloid test, has been demonstrated.

Pharmacological and clinical studies indicate that hydroxyzine in therapeutic dosage does not increase gastric secretion or acidity and in most cases has mild antisecretory activity.

Hydroxyzine is rapidly absorbed from the gastrointestinal tract and hydroxyzine's clinical effects are usually noted within 15 to 30 minutes after oral administration.

INDICATIONS AND USAGE

For symptomatic relief of anxiety and tension associated with psychoneurosis and as an adjunct in organic disease states in which anxiety is manifested.

Useful in the management of pruritus due to allergic conditions such as chronic urticaria and atopic and contact dermatoses and in histamine-mediated pruritus.

As a sedative when used as a premedication and following general anesthesia, hydroxyzine may potentiate meperidine and barbiturates, so their use in pre-anesthetic adjunctive therapy should be modified on an individual basis. Atropine and other belladonna alkaloids are not affected by the drug. Hydroxyzine is not known to interfere with the action of digitalis in any way and it may be used concurrently with this agent.

The effectiveness of hydroxyzine as an antianxiety agent for long term use, that is more than 4 months, has not been assessed by systematic clinical studies. The physician should reassess periodically the usefulness of the drug for the individual patient.

CONTRAINDICATIONS

Hydroxyzine, when administered to the pregnant mouse, rat, and rabbit induced fetal abnormalities in the rat and mouse at doses substantially above the human therapeutic range. Clinical data in human beings are inadequate to establish safety in early pregnancy. Until such data are available, hydroxyzine is contraindicated in early pregnancy.

Hydroxyzine is contraindicated for patients who have shown a previous hypersensitivity to any component of this medication.

WARNINGS

Nursing Mothers:

It is not known whether this drug is excreted in human milk. Since many drugs are so excreted, hydroxyzine should not be given to nursing mothers.

PRECAUTIONS

General:

THE POTENTIATING ACTION OF HYDROXYZINE MUST BE CONSIDERED WHEN THE DRUG IS USED IN CONJUNCTION WITH CENTRAL NERVOUS SYSTEM DEPRESSANTS SUCH AS NARCOTICS, NON-NARCOTIC ANALGESICS AND BARBITURATES. Therefore, when central nervous system depressants are administered concomitantly with hydroxyzine their dosage should be reduced.

Since drowsiness may occur with use of this drug, patients should be warned of this possibility and cautioned against driving a car or operating dangerous machinery while taking hydroxyzine. Patients should also be advised against the simultaneous use of other CNS depressant drugs, and cautioned that the effects of alcohol may be increased.

Hydroxyzine Hydrochloride Tablets 50 mg contain FD&C Yellow No. 5 (tartrazine) which may cause allergic-type reactions (including bronchial asthma) in certain susceptible persons. Although the overall incidence of FD&C Yellow No. 5 (tartrazine) sensitivity in the general population is low, it is frequently seen in patients who also have aspirin hypersensitivity.

Geriatric Use:

A determination has not been made whether controlled clinical studies of hydroxyzine included sufficient numbers of subjects aged 65 and over to define a difference in response from younger subjects. Other reported clinical experience has not identified differences in responses between the elderly and younger patients. In general, dose selection for an elderly patient should be cautious, usually starting at the low end of the dosing range, reflecting the greater frequency of decreased hepatic, renal or cardiac function, and of concomitant disease or other drug therapy.

The extent of renal excretion of hydroxyzine has not been determined. Because elderly patients are more likely to have decreased renal function, care should be taken in dose selections.

Sedating drugs may cause confusion and over sedation in the elderly; elderly patients generally should be started on low doses of hydroxyzine and observed closely.

ADVERSE REACTIONS

Side effects reported with the administration of hydroxyzine hydrochloride are usually mild and transitory in nature.

Anticholinergic: Dry mouth.

Central Nervous System: Drowsiness is usually transitory and may disappear in a few days of continued therapy or upon reduction of dose. Involuntary motor activity including rare instances of tremor and convulsions have been reported, usually with doses considerably higher than those recommended. Clinically significant respiratory depression has not been reported at recommended doses.

In post-marketing experience, the following additional undesirable effects have been reported:
Body as a Whole: allergic reaction.
Nervous System: headache.
Psychiatric: hallucination.
Skin and Appendages: pruritus, rash, urticaria.

OVERDOSAGE

The most common manifestation of hydroxyzine overdosage is hypersedation. Other reported signs and symptoms were convulsions, stupor, nausea and vomiting. As in the management of overdosage with any drug, it should be borne in mind that multiple agents may have been taken.

If vomiting has not occurred spontaneously, it should be induced. Immediate gastric lavage is also recommended. General supportive care, including frequent monitoring of the vital signs and close observation of the patient, is indicated. Hypotension, though unlikely, may be controlled with intravenous fluids and levarterenol, or metaraminol. Do not use epinephrine as hydroxyzine counteracts its pressor action.

There is no specific antidote. It is doubtful that hemodialysis would be of any value in the treatment of overdosage with hydroxyzine. However, if other agents such as barbiturates have been ingested concomitantly, hemodialysis may be indicated. There is no practical method to quantitate hydroxyzine in body fluids or tissue after its ingestion or administration.

DOSAGE AND ADMINISTRATION

For symptomatic relief of anxiety and tension associated with psychoneurosis and as an adjunct in organic disease states in which anxiety is manifested: Adults, 50–100 mg q.i.d.; children under 6 years, 50 mg daily in divided doses; children over 6 years, 50–100 mg daily in divided doses.

For use in the management of pruritus due to allergic conditions such as chronic urticaria and atopic and contact dermatoses and in histamine-mediated pruritus: adults, 25 mg t.i.d. or q.i.d.; children under 6 years, 50 mg daily in divided doses; children over 6 years, 50–100 mg daily in divided doses.

As a sedative when used as a premedication and following general anesthesia: 50–100 mg for adults and 0.6 mg/kg of body weight in children.

When treatment is initiated by the intramuscular route of administration, subsequent doses may be administered orally.

As with all potent medication, the dosage should be adjusted according to the patient's response to therapy.

HOW SUPPLIED

Hydroxyzine Hydrochloride Tablets, USP are available as:

10 mg – orange, round tablets debossed "3615" on one side and debossed "V" on the reverse side. Supplied in bottles of:

- Bottles of 10: NDC 0603-3967-10
- Bottles of 100: NDC 0603-3967-21
- Bottles of 500: NDC 0603-3967-28
- Bottles of 1000: NDC 0603-3967-32

25 mg – green, round tablets debossed "3616" on one side and debossed "V" on the reverse side. Supplied in bottles of:

- Bottles of 10: NDC 0603-3968-10
- Bottles of 100: NDC 0603-3968-21
- Bottles of 500: NDC 0603-3968-28
- Bottles of 1000: NDC 0603-3968-32

50 mg – light orange, round tablets debossed "3617" on one side and debossed "V" on the reverse side. Supplied in bottles of:

- Bottles of 10: NDC 0603-3969-10
- Bottles of 100: NDC 0603-3969-21
- Bottles of 500: NDC 0603-3969-28
- Bottles of 1000: NDC 0603-3969-32

STORAGE AND HANDLING

Dispense in a tight container as defined in the USP.

Store at 20° to 25°C (68° to 77°F) [see USP Controlled Room Temperature].

Manufactured for:
QUALITEST PHARMACEUTICALS
Huntsville, AL 35811

8181154
R2/13-R2

And Relabeled By:

Dispensing Solutions Inc.
3000 West Warner Ave
Santa Ana, CA 92704
United States

PACKAGE LABEL.PRINCIPAL DISPLAY PANEL

NDC 66336-0086-XX

NDC 66336-0086-60